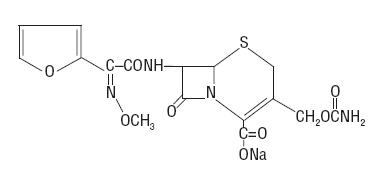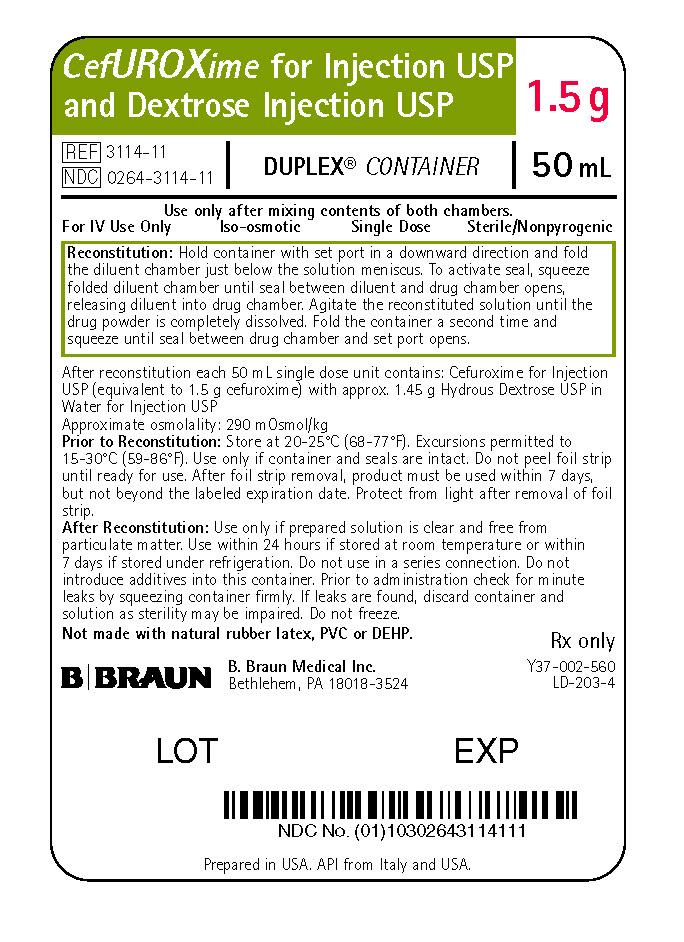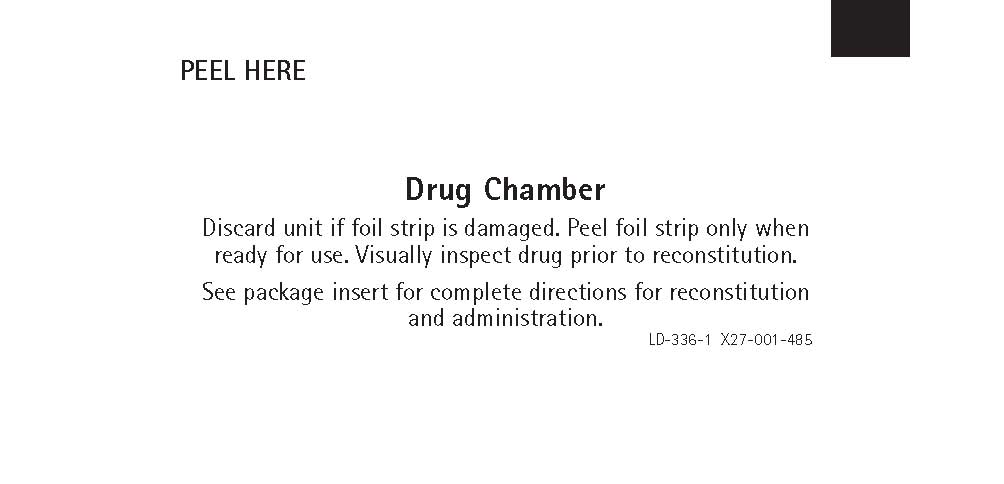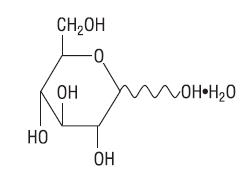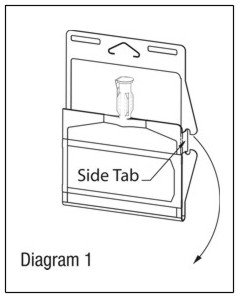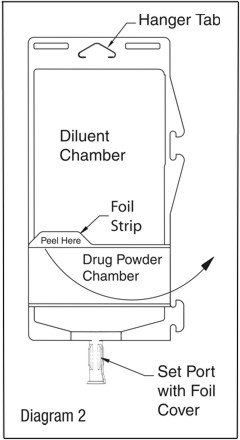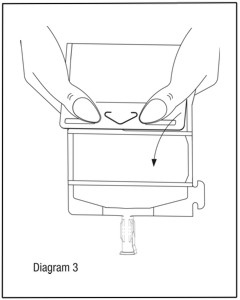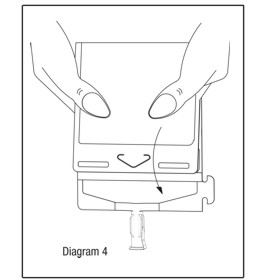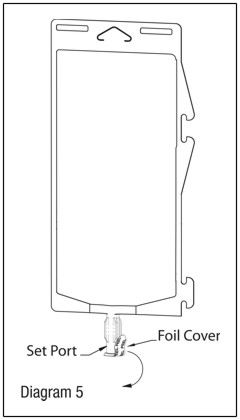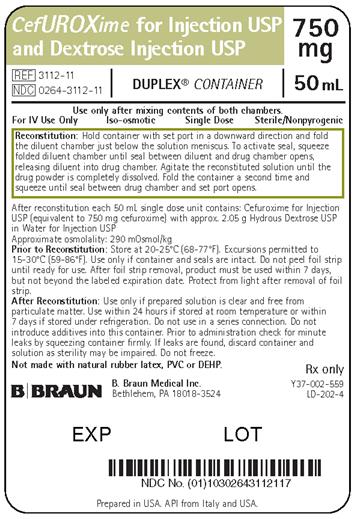 DRUG LABEL: Cefuroxime and Dextrose
NDC: 0264-3112 | Form: INJECTION, SOLUTION
Manufacturer: B. Braun Medical Inc.
Category: prescription | Type: HUMAN PRESCRIPTION DRUG LABEL
Date: 20201205

ACTIVE INGREDIENTS: CEFUROXIME SODIUM 750 mg/50 mL
INACTIVE INGREDIENTS: WATER; DEXTROSE 2.05 g/50 mL

CefUROXime for Injection USP and Dextrose Injection USP

To reduce the development of drug-resistant bacteria and maintain the effectiveness of Cefuroxime for Injection USP and Dextrose Injection USP and other antibacterial drugs, Cefuroxime for Injection USP and Dextrose Injection USP should be used only to treat or prevent infections that are proven or strongly suspected to be caused by bacteria.

DESCRIPTION

Cefuroxime for Injection USP and Dextrose Injection USP is a sterile, nonpyrogenic, single use, packaged combination of Cefuroxime Sodium USP (crystalline) and Dextrose Injection USP (diluent) in the DUPLEX® sterile container. The DUPLEX® Container is a flexible dual chamber container.

The drug chamber is filled with sterile crystalline Cefuroxime for Injection USP, a semi-synthetic, broad-spectrum, cephalosporin antibacterial for parenteral administration. It is the sodium salt of (6R,7R)-7-[2-(2-furyl)glyoxylamido]-3-(hydroxymethyl)-8-oxo-5-thia-1-azabicyclo[4.2.0]oct-2-ene-2-carboxylate, 7^2-(Z)-(O-methyloxime), carbamate (ester).

Cefuroxime Sodium USP has the following structural formula:

The empirical formula is C16H15N4NaO8S, representing a molecular weight of 446.4.

Cefuroxime contains approximately 54.2 mg (2.4 mEq) of sodium per gram of cefuroxime activity.

The diluent chamber contains Dextrose Injection USP. The concentration of Hydrous Dextrose USP has been adjusted to render the reconstituted drug product iso-osmotic. Dextrose Injection USP is sterile, nonpyrogenic, and contains no bacteriostatic or antimicrobial agents.

Hydrous Dextrose USP has the following structural (molecular) formula:

The molecular weight of Hydrous Dextrose USP is 198.17.

Dextrose hydrous USP has been added to the diluent to adjust osmolality (approximately 2.05 g and 1.45 g to 750 mg and 1.5 g dosages, respectively).

After removing the peelable foil strip, activating the seals, and thoroughly mixing, the reconstituted drug product is intended for single intravenous use. When reconstituted, the approximate osmolality of the reconstituted solution for Cefuroxime for Injection USP and Dextrose Injection USP is 290 mOsmol/kg.

Not made with natural rubber latex, PVC or Di (2-ethylhexyl) phthalate (DEHP).

The DUPLEX® dual chamber container is made from a specially formulated material. The product (diluent and drug) contact layer is a mixture of thermoplastic rubber and a polypropylene ethylene copolymer that contains no plasticizers. The safety of the container system is supported by USP biological evaluation procedures.

CLINICAL PHARMACOLOGY

Following IV doses of 750 mg and 1.5 g, serum concentrations were approximately 50 and 100 mcg/mL, respectively, at 15 minutes. Therapeutic serum concentrations of approximately 2 mcg/mL or more were maintained for 5.3 hours and 8 hours or more, respectively. There was no evidence of accumulation of cefuroxime in the serum following IV administration of 1.5 g doses every 8 hours to normal volunteers. The serum half-life after IV injection is approximately 80 minutes.

Approximately 89% of a dose of cefuroxime is excreted by the kidneys over an 8-hour period, resulting in high urinary concentrations.

Intravenous doses of 750 mg and 1.5 g produced urinary levels averaging 1,150 and 2,500 mcg/mL, respectively, during the first 8-hour period.

The concomitant oral administration of probenecid with cefuroxime slows tubular secretion, decreases renal clearance by approximately 40%, increases the peak serum level by approximately 30%, and increases the serum half-life by approximately 30%. Cefuroxime is detectable in therapeutic concentrations in pleural fluid, joint fluid, bile, sputum, bone, and aqueous humor.

Cefuroxime is detectable in therapeutic concentrations in cerebrospinal fluid (CSF) of adults and pediatric patients with meningitis. The following table shows the concentrations of cefuroxime achieved in cerebrospinal fluid during multiple dosing of patients with meningitis.

Table 1. Concentrations of Cefuroxime Achieved in Cerebrospinal Fluid During Multiple Dosing of Patients with Meningitis
Patients | Dose | Number of Patients | Mean (Range) CSF Cefuroxime Concentrations (mcg/mL) Achieved Within 8 Hours Post Dose
Pediatric patients (4 weeks to 6.5 years) | 200 mg/kg/day, divided q 6 hours | 5 | 6.6 (0.9–17.3)
Pediatric patients (7 months to 9 years) | 200 to 230 mg/kg/day, divided q 8 hours | 6 | 8.3 (<2–22.5)
Adults | 1.5 grams q 8 hours | 2 | 5.2 (2.7–8.9)
Adults | 1.5 grams q 6 hours | 10 | 6.0 (1.5–13.5)

Cefuroxime is approximately 50% bound to serum protein.

Microbiology

Mechanism of Action

Cefuroxime is a bactericidal agent that acts by inhibition of bacterial cell wall synthesis. Cefuroxime has activity in the presence of some beta-Iactamases, both penicillinases and cephalosporinases, of Gram-negative and Gram-positive bacteria.

Resistance

Resistance to cefuroxime is primarily through hydrolysis by beta-Iactamase, alteration of penicillin-binding proteins (PBPs), and decreased permeability.

Interaction with Other Antimicrobials

In an in vitro study antagonistic effects have been observed with the combination of chloramphenicol and cefuroxime.

Antimicrobial Activity

Cefuroxime has been shown to be active against most isolates of the following bacteria, both in vitro and in clinical infections as described in the INDICATIONS AND USAGE section:

Gram-negative bacteria

- Enterobacter spp.
- Escherichia coli
- Klebsiella spp.
- Haemophilus influenzae
- Neisseria meningitidis
- Neisseria gonorrhoeae

Gram-positive bacteria

- Staphylococcus aureus
- Streptococcus pneumoniae
- Streptococcus pyogenes

The following in vitro data are available, but their clinical significance is unknown. At least 90 percent of the following bacteria exhibit an in vitro minimum inhibitory concentration (MIC) less than or equal to the susceptible breakpoint for cefuroxime against isolates of similar genus or organism group. However, the efficacy of cefuroxime in treating clinical infections caused by these bacteria has not been established in adequate and well-controlled clinical trials.

Gram-negative bacteria

Citrobacter spp.
Providencia rettgeri
Haemophilus parainfluenzae
Proteus mirabilis
Moraxella catarrhalis
Morganella morganii
Salmonella spp.
Shigella spp.

Gram-positive bacteria

Staphylococcus epidermidis

Susceptibility Testing

For specific information regarding susceptibility test interpretive criteria, and associated test methods and quality control standards recognized by FDA for this drug, please see: https://www.fda.gov/STIC.

INDICATIONS AND USAGE

Cefuroxime for Injection USP and Dextrose Injection USP is indicated for the treatment of patients with infections caused by susceptible strains of the designated organisms in the following diseases:

1. Lower Respiratory Tract Infections, including pneumonia, caused by Streptococcus pneumoniae, Haemophilus influenzae (including ampicillin-resistant strains), Klebsiella spp., Staphylococcus aureus (penicillinase- and non-penicillinase-producing strains), Streptococcus pyogenes, and Escherichia coli.
2. Urinary Tract Infections caused by Escherichia coli and Klebsiella spp.
3. Skin and Skin-Structure Infections caused by Staphylococcus aureus (penicillinase- and non-penicillinase-producing strains), Streptococcus pyogenes, Escherichia coli, Klebsiella spp., and Enterobacter spp.
4. Septicemia caused by Staphylococcus aureus (penicillinase- and non-penicillinase-producing strains), Streptococcus pneumoniae, Escherichia coli, Haemophilus influenzae (including ampicillin-resistant strains), and Klebsiella spp.
5. Meningitis caused by Streptococcus pneumoniae, Haemophilus influenzae (including ampicillin-resistant strains), Neisseria meningitidis, and Staphylococcus aureus (penicillinase- and non-penicillinase-producing strains).
6. Gonorrhea: Uncomplicated and disseminated gonococcal infections due to Neisseria gonorrhoeae (penicillinase- and non-penicillinase-producing strains) in both males and females.
7. Bone and Joint Infections caused by Staphylococcus aureus (penicillinase- and non-penicillinase producing strains).

Clinical microbiological studies in skin and skin-structure infections frequently reveal the growth of susceptible strains of both aerobic and anaerobic organisms. Cefuroxime has been used successfully in these mixed infections in which several organisms have been isolated.

In certain cases of confirmed or suspected gram-positive or gram-negative sepsis or in patients with other serious infections in which the causative organism has not been identified, cefuroxime may be used concomitantly with an aminoglycoside (see PRECAUTIONS). The recommended doses of both antibacterials may be given depending on the severity of the infection and the patient's condition.

To reduce the development of drug-resistant bacteria and maintain the effectiveness of Cefuroxime for Injection USP and Dextrose Injection USP and other antibacterial drugs, Cefuroxime for Injection USP and Dextrose Injection USP should be used only to treat or prevent infections that are proven or strongly suspected to be caused by susceptible bacteria. When culture and susceptibility information are available, they should be considered in selecting or modifying antibacterial therapy. In the absence of such data, local epidemiology and susceptibility patterns may contribute to the empiric selection of therapy.

Prevention:

The preoperative prophylactic administration of Cefuroxime for Injection USP and Dextrose Injection USP may prevent the growth of susceptible disease-causing bacteria and thereby may reduce the incidence of certain postoperative infections in patients undergoing surgical procedures (e.g., vaginal hysterectomy) that are classified as clean-contaminated or potentially contaminated procedures. Effective prophylactic use of antibacterials in surgery depends on the time of administration. Cefuroxime for Injection USP and Dextrose Injection USP should usually be given one-half to 1 hour before the operation to allow sufficient time to achieve effective antibacterial concentrations in the wound tissues during the procedure. The dose should be repeated intraoperatively if the surgical procedure is lengthy.

Prophylactic administration is usually not required after the surgical procedure ends and should be stopped within 24 hours. In the majority of surgical procedures, continuing prophylactic administration of any antibacterial does not reduce the incidence of subsequent infections but will increase the possibility of adverse reactions and the development of bacterial resistance.

The perioperative use of Cefuroxime for Injection USP and Dextrose Injection USP has also been effective during open heart surgery for surgical patients in whom infections at the operative site would present a serious risk. For these patients it is recommended that cefuroxime therapy be continued for at least 48 hours after the surgical procedure ends. If an infection is present, specimens for culture should be obtained for the identification of the causative organism, and appropriate antimicrobial therapy should be instituted.

CONTRAINDICATIONS

Cefuroxime for Injection USP and Dextrose Injection USP is contraindicated in patients with known allergy to the cephalosporin group of antibacterials.

Solutions containing dextrose may be contraindicated in patients with hypersensitivity to corn products.

WARNINGS

BEFORE THERAPY WITH CEFUROXIME FOR INJECTION USP AND DEXTROSE INJECTION USP IS INSTITUTED, CAREFUL INQUIRY SHOULD BE MADE TO DETERMINE WHETHER THE PATIENT HAS HAD PREVIOUS HYPERSENSITIVITY REACTIONS TO CEPHALOSPORINS, PENICILLINS OR OTHER DRUGS. THIS PRODUCT SHOULD BE GIVEN CAUTIOUSLY TO PENICILLIN-SENSITIVE PATIENTS. ANTIBACTERIALS SHOULD BE ADMINISTERED WITH CAUTION TO ANY PATIENT WHO HAS DEMONSTRATED SOME FORM OF ALLERGY, PARTICULARLY TO DRUGS. IF AN ALLERGIC REACTION TO CEFUROXIME OCCURS, DISCONTINUE THE DRUG. SERIOUS ACUTE HYPERSENSITIVITY REACTIONS MAY REQUIRE EPINEPHRINE AND OTHER EMERGENCY MEASURES.

Clostridioides difficile associated diarrhea (CDAD) has been reported with use of nearly all antibacterial agents, including Cefuroxime for Injection USP and Dextrose Injection USP, and may range in severity from mild diarrhea to fatal colitis. Treatment with antibacterial agents alters the normal flora of the colon leading to overgrowth of C. difficile.

C. difficile produces toxins A and B which contribute to the development of CDAD. Hypertoxin producing strains of C. difficile cause increased morbidity and mortality, as these infections can be refractory to antimicrobial therapy and may require colectomy. CDAD must be considered in all patients who present with diarrhea following antibacterial use. Careful medical history is necessary since CDAD has been reported to occur over two months after the administration of antibacterial agents.

If CDAD is suspected or confirmed, ongoing antibacterial use not directed against C. difficile may need to be discontinued. Appropriate fluid and electrolyte management, protein supplementation, antibacterial treatment of C. difficile, and surgical evaluation should be instituted as clinically indicated.

PRECAUTIONS

General

Although Cefuroxime for Injection USP and Dextrose Injection USP rarely produces alterations in kidney function, evaluation of renal status during therapy is recommended, especially in seriously ill patients receiving the maximum doses. Cephalosporins should be given with caution to patients receiving concurrent treatment with potent diuretics as these regimens are suspected of adversely affecting renal function.

The total daily dose of cefuroxime should be reduced in patients with transient or persistent renal insufficiency (see DOSAGE AND ADMINISTRATION), because high and prolonged serum antibacterial concentrations can occur in such individuals from usual doses.

As with other antibacterials, prolonged use of cefuroxime may result in overgrowth of nonsusceptible organisms. Careful observation of the patient is essential. If superinfection occurs during therapy, appropriate measures should be taken.

Broad-spectrum antibacterials should be prescribed with caution in individuals with a history of gastrointestinal disease, particularly colitis.

Nephrotoxicity has been reported following concomitant administration of aminoglycoside antibacterials and cephalosporins.

As with other therapeutic regimens used in the treatment of meningitis, mild-to-moderate hearing loss has been reported in a few pediatric patients treated with cefuroxime. Persistence of positive CSF (cerebrospinal fluid) cultures at 18 to 36 hours has also been noted with cefuroxime injection, as well as with other antibacterial therapies; however, the clinical relevance of this is unknown.

Cephalosporins may be associated with a fall in prothrombin activity. Those at risk include patients with renal or hepatic impairment, or poor nutritional state, as well as patients receiving a protracted course of antimicrobial therapy, and patients previously stabilized on anticoagulant therapy. Prothrombin time should be monitored in patients at risk and exogenous Vitamin K administered as indicated.

As with other dextrose-containing solutions, Cefuroxime for Injection USP and Dextrose Injection USP should be prescribed with caution in patients with overt or known subclinical diabetes mellitus or carbohydrate intolerance for any reason.

Prescribing Cefuroxime for Injection USP and Dextrose Injection USP in the absence of a proven or strongly suspected bacterial infection or a prophylactic indication is unlikely to provide benefit to the patient and increases the risk of the development of drug-resistant bacteria.

Information for Patients

Diarrhea is a common problem caused by antibacterials which usually ends when the antibacterial is discontinued. Sometimes after starting treatment with antibacterials, patients can develop watery and bloody stools (with or without stomach cramps and fever) even as late as two or more months after having taken the last dose of the antibacterial. If this occurs, patients should contact their physician as soon as possible.

Patients should be counseled that antibacterial drugs including Cefuroxime for Injection USP and Dextrose Injection USP should only be used to treat bacterial infections. They do not treat viral infections (e.g., the common cold). When Cefuroxime for Injection USP and Dextrose Injection USP is prescribed to treat a bacterial infection, patients should be told that although it is common to feel better early in the course of therapy, the medication should be taken exactly as directed. Skipping doses or not completing the full course of therapy may (1) decrease the effectiveness of the immediate treatment and (2) increase the likelihood that bacteria will develop resistance and will not be treatable by Cefuroxime for Injection USP and Dextrose Injection USP or other antibacterial drugs in the future.

Drug/Laboratory Test Interactions

A false-positive reaction for glucose in the urine may occur with copper reduction tests (Benedict's or Fehling's solution or with Clinitest® tablets) but not with enzyme-based tests for glycosuria. As a false-negative result may occur in the ferricyanide test, it is recommended that either the glucose oxidase or hexokinase method be used to determine blood plasma glucose levels in patients receiving cefuroxime.

Cefuroxime does not interfere with the assay of serum and urine creatinine by the alkaline picrate method.

Carcinogenesis, Mutagenesis, Impairment of Fertility

Although lifetime studies in animals have not been performed to evaluate carcinogenic potential, no mutagenic activity was found for cefuroxime in the mouse lymphoma assay and a battery of bacterial mutation tests. Positive results were obtained in an in vitro chromosome aberration assay, however, negative results were found in an in vivo micronucleus test at doses up to 10 g/kg. Reproduction studies in mice at doses up to 3,200 mg/kg/day (3.1 times the recommended maximum human dose based on mg/m^2) have revealed no impairment of fertility.

Reproductive studies revealed no impairment of fertility in animals.

Pregnancy

Teratogenic Effects

Reproduction studies have been performed in mice at doses up to 6,400 mg/kg/day (6.3 times the recommended maximum human dose based on mg/m^2), and rabbits at doses up to 400 mg/kg/day (2.1 times the recommended maximum human dose based on mg/m^2) and have revealed no evidence of impaired fertility or harm to the fetus due to cefuroxime. There are, however, no adequate and well-controlled studies in pregnant women. Because animal reproduction studies are not always predictive of human response, this drug should be used during pregnancy only if clearly needed.

Nursing Mothers

Since cefuroxime is excreted in human milk, caution should be exercised when cefuroxime is administered to a nursing woman.

Pediatric Use

Safety and effectiveness in pediatric patients below 3 months of age have not been established. Accumulation of other members of the cephalosporin class in newborn infants (with resulting prolongation of drug half-life) has been reported.

Cefuroxime for Injection USP and Dextrose Injection USP in the DUPLEX® Container is designed to deliver a 750 mg or 1.5 g dose of cefuroxime. To prevent unintentional overdose, this product should not be used in pediatric patients who require less than the full adult dose of cefuroxime.

Geriatric Use

Of the 1,914 subjects who received cefuroxime in 24 clinical studies of cefuroxime, 901 (47%) were 65 and over while 421 (22%) were 75 and over. No overall differences in safety or effectiveness were observed between these subjects and younger subjects, and other reported clinical experience has not identified differences in responses between the elderly and younger patients, but greater susceptibility of some older individuals to drug effects cannot be ruled out. This drug is known to be substantially excreted by the kidney, and the risk of toxic reactions to this drug may be greater in patients with impaired renal function. Because elderly patients are more likely to have decreased renal function, care should be taken in dose selection, and it may be useful to monitor renal function (see DOSAGE AND ADMINISTRATION).

ADVERSE REACTIONS

Cefuroxime is generally well tolerated. The most common adverse effects have been local reactions following IV administration. Other adverse reactions have been encountered only rarely.

Local Reactions:

Thrombophlebitis has occurred with IV administration in 1 in 60 patients.

Gastrointestinal:

Gastrointestinal symptoms occurred in 1 in 150 patients and included diarrhea (1 in 220 patients) and nausea (1 in 440 patients). The onset of pseudomembranous colitis may occur during or after antibacterial treatment (see WARNINGS).

Hypersensitivity Reactions:

Hypersensitivity reactions have been reported in fewer than 1% of the patients treated with cefuroxime and include rash (1 in 125). Pruritus, urticaria, and positive Coombs' test each occurred in fewer than 1 in 250 patients, and, as with other cephalosporins, rare cases of anaphylaxis, drug fever, erythema multiforme, interstitial nephritis, toxic epidermal necrolysis, and Stevens-Johnson syndrome have occurred.

Blood:

A decrease in hemoglobin and hematocrit has been observed in 1 in 10 patients and transient eosinophilia in 1 in 14 patients. Less common reactions seen were transient neutropenia (fewer than 1 in 100 patients) and leukopenia (1 in 750 patients). A similar pattern and incidence were seen with other cephalosporins used in controlled studies. As with other cephalosporins, there have been rare reports of thrombocytopenia.

Hepatic:

Transient rise in SGOT and SGPT (1 in 25 patients), alkaline phosphatase (1 in 50 patients), LDH (1 in 75 patients), and bilirubin (1 in 500 patients) levels has been noted.

Kidney:

Elevations in serum creatinine and/or blood urea nitrogen and a decreased creatinine clearance have been observed, but their relationship to cefuroxime is unknown.

Postmarketing Experience with Cefuroxime:

In addition to the adverse events reported during clinical trials, the following events have been observed during clinical practice in patients treated with cefuroxime and were reported spontaneously. Data are generally insufficient to allow an estimate of incidence or to establish causation.

Immune System Disorders:

Angioedema, acute myocardial ischemia with or without myocardial infarction may occur as part of an allergic reaction.

Neurologic System Disorders:

Seizure.

Cephalosporin-class Adverse Reactions:

In addition to the adverse reactions listed above that have been observed in patients treated with cefuroxime, the following adverse reactions and altered laboratory tests have been reported for cephalosporin-class antibacterials:

Adverse Reactions:

Vomiting, abdominal pain, colitis, vaginitis including vaginal candidiasis, toxic nephropathy, hepatic dysfunction including cholestasis, aplastic anemia, hemolytic anemia, and hemorrhage.

Several cephalosporins, including cefuroxime, have been implicated in triggering seizures, particularly in patients with renal impairment when the dosage was not reduced (see DOSAGE AND ADMINISTRATION). If seizures associated with drug therapy should occur, the drug should be discontinued. Anticonvulsant therapy can be given if clinically indicated.

Altered Laboratory Tests:

Prolonged prothrombin time, pancytopenia, agranulocytosis.

OVERDOSAGE

Overdosage of cephalosporins can cause cerebral irritation leading to convulsions. Serum levels of cefuroxime can be reduced by hemodialysis and peritoneal dialysis.

DOSAGE AND ADMINISTRATION

This product is intended for intravenous administration only.

Dosage:

Adults:

The usual adult dosage range for cefuroxime is 750 mg to 1.5 grams every 8 hours, usually for 5 to 10 days. In uncomplicated urinary tract infections, skin and skin-structure infections, disseminated gonococcal infections, and uncomplicated pneumonia, a 750 mg dose every 8 hours is recommended. In severe or complicated infections, a 1.5 gram dose every 8 hours is recommended.

In bone and joint infections, a 1.5 gram dose every 8 hours is recommended. In clinical trials, surgical intervention was performed when indicated as an adjunct to cefuroxime therapy. A course of oral antibacterials was administered when appropriate following the completion of parenteral administration of cefuroxime.

In life-threatening infections or infections due to less susceptible organisms, 1.5 grams every 6 hours may be required. In bacterial meningitis, the dosage should not exceed 3 grams every 8 hours. For preventive use for clean-contaminated or potentially contaminated surgical procedures, a 1.5 gram dose administered intravenously just before surgery (approximately one-half to 1 hour before the initial incision) is recommended. Thereafter, give 750 mg intravenously every 8 hours when the procedure is prolonged.

For preventive use during open heart surgery, a 1.5 gram dose administered intravenously at the induction of anesthesia and every 12 hours thereafter for a total of 6 grams is recommended.

Impaired Renal Function:

A reduced dosage must be employed when renal function is impaired. Dosage should be determined by the degree of renal impairment and the susceptibility of the causative organism (see Table 2).

Table 2: Dosage of Cefuroxime in Adults with Reduced Renal Function
Creatinine Clearance (mL/min) | Dose | Frequency
>20 | 750 mg–1.5 grams | q8h
10–20 | 750 mg | q12h
<10 | 750 mg | q24h [Since cefuroxime is dialyzable, patients on hemodialysis should be given a further dose at the end of the dialysis.]

When only serum creatinine is available, the following formula^1 (based on sex, weight, and age of the patient) may be used to convert this value into creatinine clearance. The serum creatinine should represent a steady state of renal function.

Males: Creatinine clearance (mL/min) = | Weight (kg) × (140 - age) 72 × serum creatinine (mg/dL)
Females: 0.85 × male value

Note: As with antibacterial therapy in general, administration of Cefuroxime for Injection USP and Dextrose Injection USP should be continued for a minimum of 48 to 72 hours after the patient becomes asymptomatic or after evidence of bacterial eradication has been obtained; a minimum of 10 days of treatment is recommended in infections caused by Streptococcus pyogenes in order to guard against the risk of rheumatic fever or glomerulonephritis; frequent bacteriologic and clinical appraisal is necessary during therapy of chronic urinary tract infection and may be required for several months after therapy has been completed; persistent infections may require treatment for several weeks; and doses smaller than those indicated above should not be used. In staphylococcal and other infections involving a collection of pus, surgical drainage should be carried out where indicated.

Pediatric Patients Above 3 Months of Age:

Administration of 50 to 100 mg/kg/day in equally divided doses every 6 to 8 hours has been successful for most infections susceptible to cefuroxime. The higher dosage of 100 mg/kg/day (not to exceed the maximum adult dosage) should be used for the more severe or serious infections.

In bone and joint infections, 150 mg/kg/day (not to exceed the maximum adult dosage) is recommended in equally divided doses every 8 hours. In clinical trials, a course of oral antibacterials was administered to pediatric patients following the completion of parenteral administration of cefuroxime.

In cases of bacterial meningitis, a larger dosage of cefuroxime is recommended, 200 to 240 mg/kg/day intravenously in divided doses every 6 to 8 hours.

In pediatric patients with renal insufficiency, the frequency of dosing should be modified consistent with the recommendations for adults.

Cefuroxime for Injection USP and Dextrose for Injection USP in the DUPLEX® Container is designed to deliver a 750 mg or 1.5 g dose of cefuroxime. To prevent unintentional overdose, this product should not be used in pediatric patients who require less than the full adult dose.

For intermittent IV infusion with a Y-type administration set, dosing can be accomplished through the tubing system by which the patient may be receiving other IV solutions. However, during infusion of the solution containing Cefuroxime, it is advisable to temporarily discontinue administration of any other solutions at the same site.

Solutions of cefuroxime, like those of most beta-lactam antibacterials, should not be added to solutions of aminoglycoside antibacterials because of potential interaction.

However, if concurrent therapy with cefuroxime and an aminoglycoside is indicated, each of these antibacterials can be administered separately to the same patient.

Use sterile equipment.

Caution: Do not use plastic containers in series connections. Such use could result in air embolism due to residual air being drawn from the primary container before administration of the fluid from the secondary container is complete.

DUPLEX® Container Directions for Use

- To avoid inadvertent activation, DUPLEX® Container should remain in the folded position until activation is intended.

Patient Labeling and Drug Powder/Diluent Inspection

- Apply patient-specific label on foil side of container. USE CARE to avoid activation. Do not cover any portion of foil strip with patient label.
- Unlatch side tab and unfold DUPLEX® Container. (See Diagram 1.)

- Visually inspect diluent chamber for particulate matter.
- Use only if container and seals are intact.
- To inspect the drug powder for foreign matter or discoloration, peel foil strip from drug chamber. (See Diagram 2.)

- Protect from light after removal of foil strip.
  Note: If foil strip is removed, product must be used within 7 days, but not beyond the labeled expiration date.
- The product should be re-folded and the side tab latched until ready to activate.

Reconstitution (Activation)

- Do not use directly after storage by refrigeration, allow the product to equilibrate to room temperature before patient use.
- Unfold the DUPLEX® Container and point the set port in a downward direction. Starting at the hanger tab end, fold the DUPLEX® Container just below the diluent meniscus trapping all air above the fold. To activate, squeeze the folded diluent chamber until the seal between the diluent and powder opens, releasing diluent into the drug powder chamber. (See Diagram 3.)

- Agitate the liquid-powder mixture until the drug powder is completely dissolved.
  Note: Following reconstitution (activation), product must be used within 24 hours if stored at room temperature or within 7 days if stored under refrigeration.

Administration

- Visually inspect the reconstituted solution for particulate matter.
- Point the set port in a downwards direction. Starting at the hanger tab end, fold the DUPLEX® Container just below the solution meniscus trapping all air above the fold. Squeeze the folded DUPLEX® Container until the seal between reconstituted drug solution and set port opens, releasing liquid to set port. (See Diagram 4.)

- Prior to attaching the IV set, check for minute leaks by squeezing container firmly. If leaks are found, discard container and solution as sterility may be impaired.
- Using aseptic technique, peel foil cover from the set port and attach sterile administration set. (See Diagram 5.)

- Refer to Directions for Use accompanying the administration set.

Precautions

- As with other cephalosporins, reconstituted Cefuroxime for Injection USP and Dextrose Injection USP tends to darken depending on storage conditions, within the stated recommendations. However, product potency is not adversely affected.
- Use only if prepared solution is clear and free from particulate matter.
- Do not use in series connection.
- Do not introduce additives into the DUPLEX® Container.
- Do not freeze.

HOW SUPPLIED

Cefuroxime for Injection USP and Dextrose Injection USP in the DUPLEX® Container is a flexible dual chamber container supplied in two concentrations. After reconstitution, the concentrations are equivalent to 750 mg and 1.5 g cefuroxime. The diluent chamber contains approximately 50 mL of Dextrose Injection USP. Dextrose Injection USP has been adjusted to 4.1% and 2.9% for the 750 mg and 1.5 g doses, respectively, such that the reconstituted solution is iso-osmotic.

Cefuroxime for Injection USP and Dextrose Injection USP is supplied sterile and nonpyrogenic in the DUPLEX® containers packaged 24 units per case.

NDC | REF | Dose | Volume
Cefuroxime for Injection USP and Dextrose Injection USP
0264-3112-11 | 3112-11 | 750 mg | 50 mL
Cefuroxime for Injection USP and Dextrose Injection USP
0264-3114-11 | 3114-11 | 1.5 g | 50 mL

STORAGE AND HANDLING

Store the unactivated unit at 20–25°C (68–77°F). Excursions permitted to 15–30°C (59–86°F).

Rx only

REFERENCES

1. Cockcroft DW, Gault MH. Prediction of creatinine clearance from serum creatinine. Nephron. 1976;16:31-41.

DUPLEX is a registered trademark of B. Braun Medical Inc.

ATCC is a registered trademark of American Type Culture Collection.

Clinitest is a registered trademark of Siemens Medical Solutions Diagnostics.

Revised: December 2020

B. Braun Medical Inc.
Bethlehem, PA 18018-3524 USA
1-800-227-2862

Prepared in USA. API from Italy and USA.

Y36-002-995 LD-194-4

PRINCIPAL DISPLAY PANEL - 750 mg Container Label

CefUROXime for Injection USP
and Dextrose Injection USP

750 mg

REF 3112-11
NDC 0264-3112-11

DUPLEX® CONTAINER
50 mL

Use only after mixing contents of both chambers.

For IV Use Only Iso-osmotic Single Dose Sterile/Nonpyrogenic

Reconstitution: Hold container with set port in a downward direction and fold the diluent chamber just below the solution meniscus. To activate seal, squeeze folded diluent chamber until seal between diluent and drug chamber opens, releasing diluent into drug chamber. Agitate the reconstituted solution until the drug powder is completely dissolved. Fold the container a second time and squeeze until seal between drug chamber and set port opens.

After reconstitution each 50 mL single dose unit contains: Cefuroxime for Injection USP (equivalent to 750 mg cefuroxime) with approx. 2.05 g Hydrous Dextrose USP in Water for Injection USP

Approximate osmolality: 290 mOsmol/kg

Prior to Reconstitution: Store at 20-25°C (68-77°F). Excursions permitted to 15-30°C (59-86°F). Use only if container and seals are intact. Do not peel foil strip until ready for use. After foil strip removal, product must be used within 7 days, but not beyond the labeled expiration date. Protect from light after removal of foil strip.

After Reconstitution: Use only if prepared solution is clear and free from particulate matter. Use within 24 hours if stored at room temperature or within 7 days if stored under refrigeration. Do not use in a series connection. Do not introduce additives into this container. Prior to administration check for minute leaks by squeezing container firmly. If leaks are found, discard container and solution as sterility may be impaired. Do not freeze.

Not made with natural rubber latex, PVC or DEHP.

Rx only

B. Braun Medical Inc.
Bethlehem, PA 18018-3524

Y37-002-559 LD-202-4

Prepared in USA. API from Italy and USA.

PEEL HERE

Drug Chamber

Discard unit if foil strip is damaged. Peel foil strip only when ready for use. Visually inspect drug prior to reconstitution.

See package insert for complete directions for reconstitution and administration.

LD-336-1 X27-001-485

PRINCIPAL DISPLAY PANEL - 1.5 g Container Label

CefUROXime for Injection USP
and Dextrose Injection USP

1.5 g

REF 3114-11
NDC 0264-3114-11
DUPLEX® CONTAINER
50 mL

Use only after mixing contents of both chambers.

For IV Use Only iso-osmotic Single Dose Sterile/Nonpyrogenic

Reconstitution: Hold container with set port in a downward direction and fold the diluent chamber just below the solution meniscus. To activate seal, squeeze folded diluent chamber until seal between diluent and drug chamber opens, releasing diluent into drug chamber. Agitate the reconstituted solution until the drug powder is completely dissolved. Fold the container a second time and squeeze until seal between drug chamber and set port opens.

After reconstitution each 50 mL single dose unit contains: Cefuroxime for Injection USP (equivalent to 1.5 g cefuroxime) with approx. 1.45 g Hydrous Dextrose USP in Water for Injection USP

Approximate osmolality: 290 mOsmol/kg

Prior to Reconstitution: Store at 20-25°C (68-77°F). Excursions permitted to 15-30°C (59-86°F). Use only if container and seals are intact. Do not peel foil strip until ready for use. After foil strip removal, product must be used within 7 days, but not beyond the labeled expiration date. Protect from light after removal of foil strip.

After Reconstitution: Use only if prepared solution is clear and free from particulate matter. Use within 24 hours if stored at room temperature or within 7 days if stored under refrigeration. Do not use in a series connection. Do not introduce additives into this container. Prior to administration check for minute leaks by squeezing container firmly. If leaks are found, discard container and solution as sterility may be impaired. Do not freeze.

Not made with natural rubber latex, PVC or DEHP.

Rx only

B. Braun Medical Inc.
Bethlehem, PA 18018-3524

Y37-002-560 LD-203-4

Prepared in USA. API from Italy and USA.

PEEL HERE

Drug Chamber

Discard unit if foil strip is damaged. Peel foil strip only when ready for use. Visually inspect drug prior to reconstitution.

See package insert for complete directions for reconstitution and administration.

LD-336-1 X27-001-485